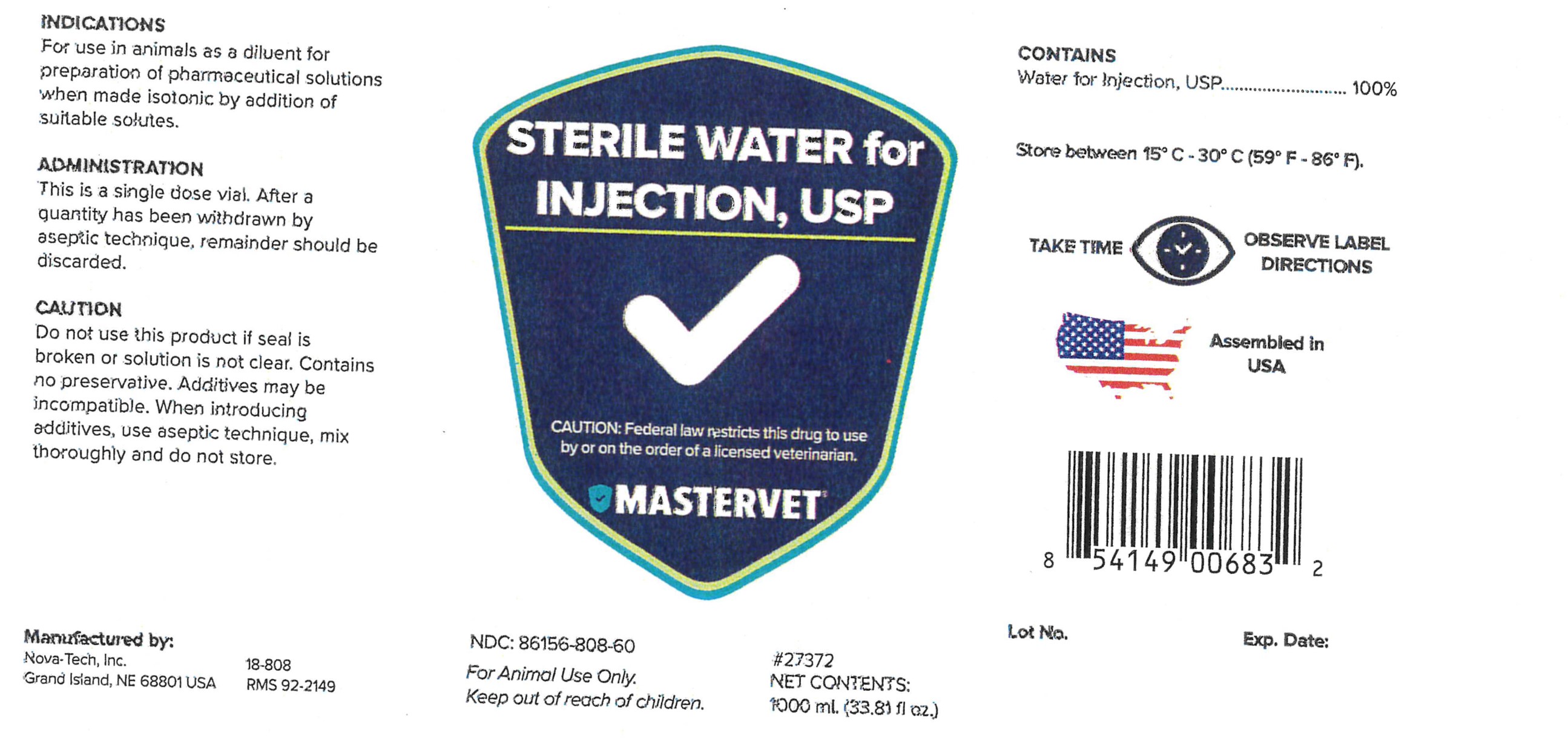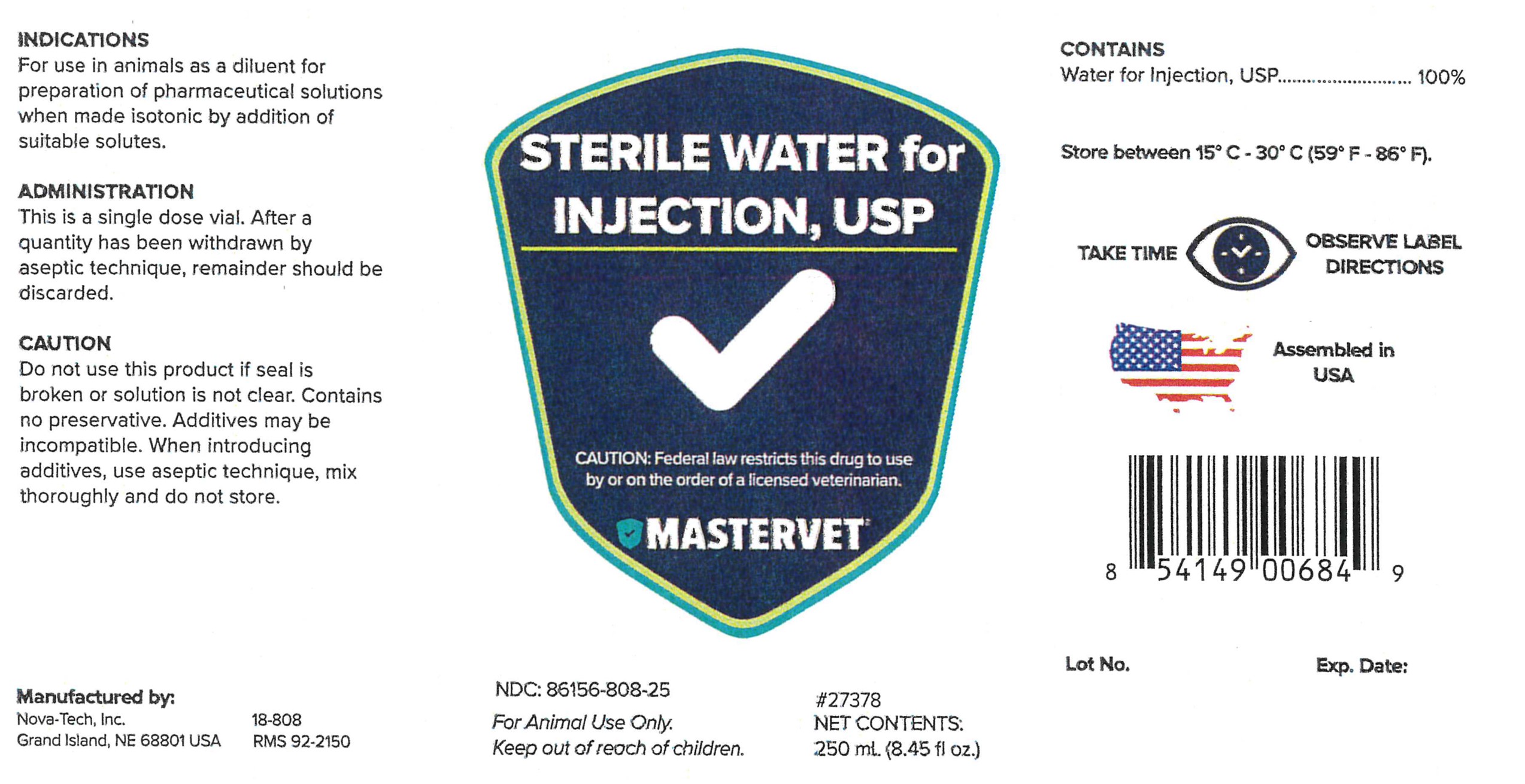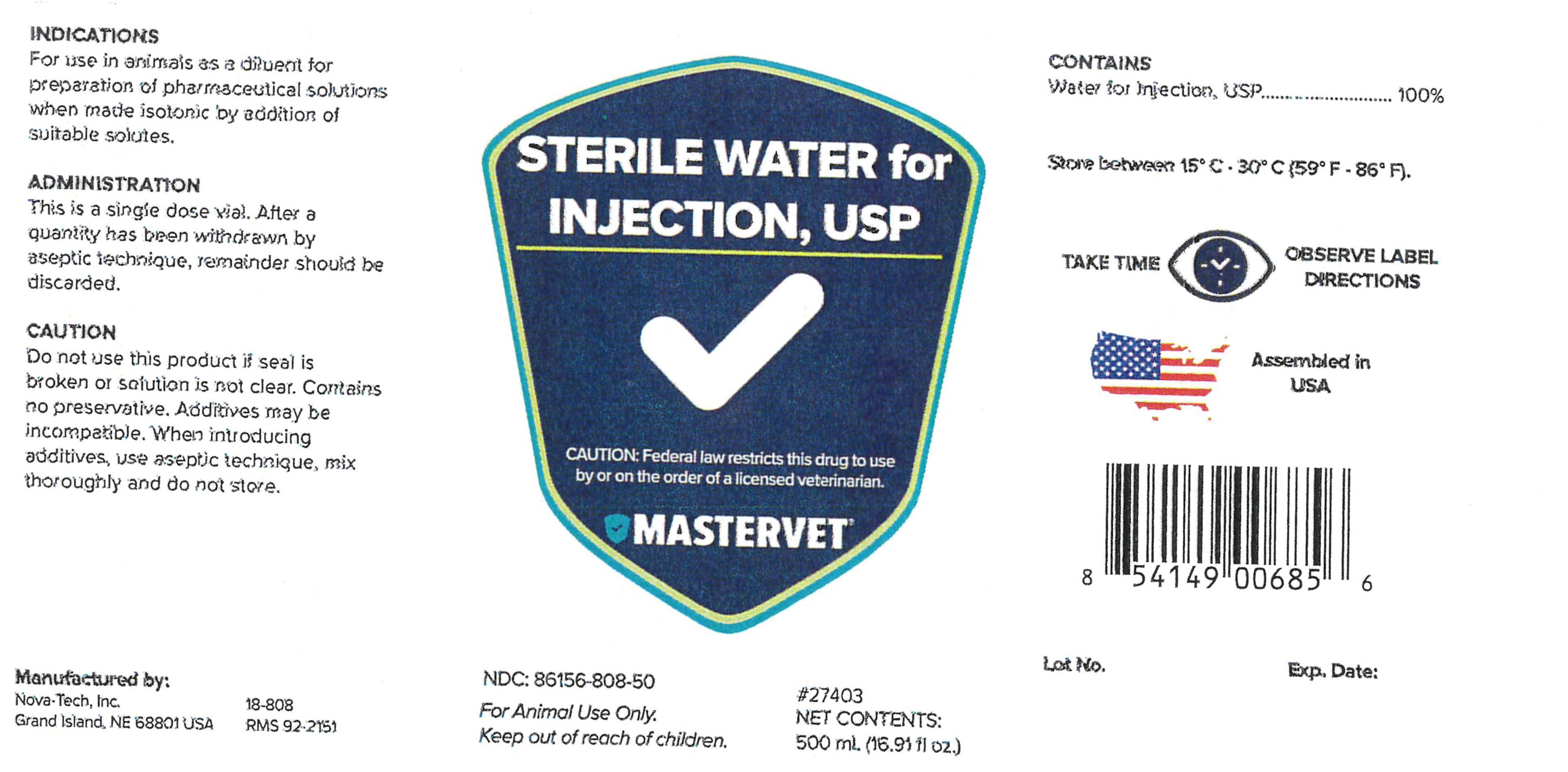 DRUG LABEL: Sterile Water
NDC: 86156-808 | Form: INJECTION
Manufacturer: MasterVet
Category: animal | Type: PRESCRIPTION ANIMAL DRUG LABEL
Date: 20230109

ACTIVE INGREDIENTS: WATER 1000 mL/1000 mL

Sterile Water For Injection, USP

CAUTION

Do not use this product if seal is broken or solution is not clear. Contains no preservative. Additives may be incompatible. When introducing additives, use aseptic technique, mix thoroughly and do not store.

CONTAINS

Water For Injection, USP.................100%

GENERAL PRECAUTIONS

TAKE TIME OBSERVE LABEL DIRECTIONS

INFORMATION FOR OWNERS/CAREGIVERS

Manufactured by:

Nova-Tech, Inc.

Grand Island, NE 68801 USA

18-808

#27372

Assembled in USA

Lot No.

Exp. Date:

GENERAL PRECAUTIONS

FOR ANIMAL USE ONLY.

KEEP OUT OF REACH OF CHILDREN.

CAUTION:

Federal law restricts this drug to use by or on the order of a licensed veterinarian.

Indications

For use in animals as a diluent for preparation of pharmaceutical solutions when made isotonic by addition of suitable solutes.

Administration

This is a single dose vial. After a quantity has been withdrawn by aseptic technique, remainder should be discarded.

STORAGE AND HANDLING

Store between 15°C - 30°C (59°F - 86°F).